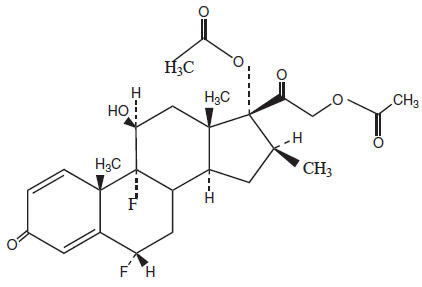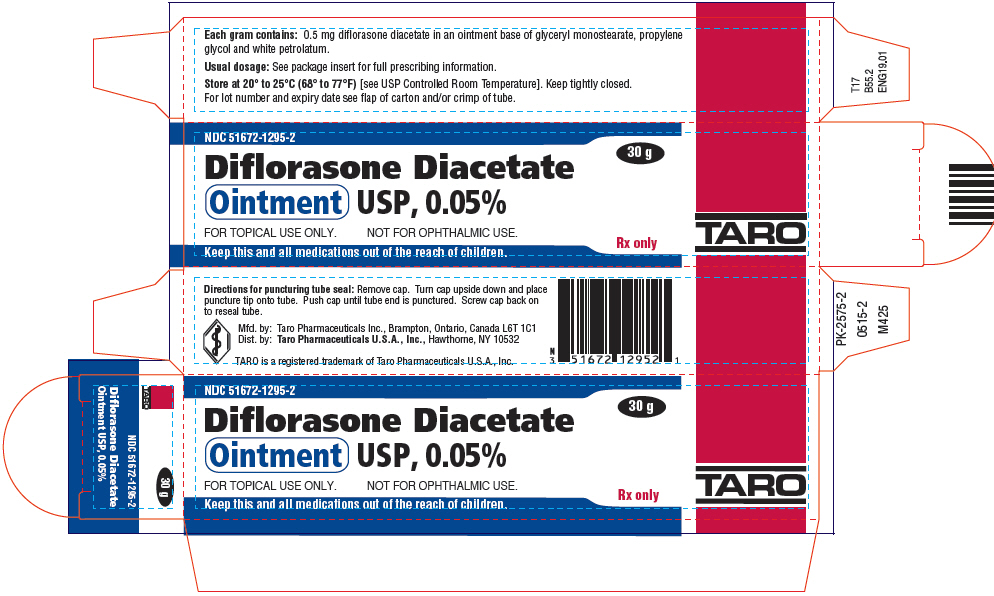 DRUG LABEL: Diflorasone Diacetate
NDC: 51672-1295 | Form: OINTMENT
Manufacturer: Sun Pharmaceutical Industries, Inc.
Category: prescription | Type: HUMAN PRESCRIPTION DRUG LABEL
Date: 20250703

ACTIVE INGREDIENTS: DIFLORASONE DIACETATE 0.5 mg/1 g
INACTIVE INGREDIENTS: PROPYLENE GLYCOL; GLYCERYL MONOSTEARATE; PETROLATUM

Diflorasone Diacetate
Ointment USP, 0.05%

Rx only

For Topical Use Only - Not for Ophthalmic Use.

DESCRIPTION

Each gram of diflorasone diacetate ointment contains 0.5 mg diflorasone diacetate in an ointment base.

Chemically, diflorasone diacetate is 6α,9-difluoro-11β,17,21-trihydroxy-16β-methylpregna-1,4-diene-3,20-dione 17,21-diacetate. The structural formula is represented below:

molecular formula:
C26H32F2O7
molecular weight:
494.54

Each gram of diflorasone diacetate ointment contains 0.5 mg diflorasone diacetate in an ointment base of glyceryl monostearate, propylene glycol and white petrolatum.

CLINICAL PHARMACOLOGY

Topical corticosteroids share anti-inflammatory, antipruritic and vasoconstrictive actions.

MECHANISM OF ACTION

The mechanism of anti-inflammatory activity of the topical corticosteroids is unclear. Various laboratory methods, including vasoconstrictor assays, are used to compare and predict potencies and/or clinical efficacies of the topical corticosteroids. There is some evidence to suggest that a recognizable correlation exists between vasoconstrictor potency and therapeutic efficacy in man.

Pharmacokinetics

The extent of percutaneous absorption of topical corticosteroids is determined by many factors including the vehicle, the integrity of the epidermal barrier, and the use of occlusive dressings.

Topical corticosteroids can be absorbed from normal intact skin. Inflammation and/or other disease processes in the skin increase percutaneous absorption. Occlusive dressings substantially increase the percutaneous absorption of topical corticosteroids. Thus, occlusive dressings may be a valuable therapeutic adjunct for treatment of resistant dermatoses. (See DOSAGE AND ADMINISTRATION.)

Once absorbed through the skin, topical corticosteroids are handled through pharmacokinetic pathways similar to systemically administered corticosteroids. Corticosteroids are bound to plasma proteins in varying degrees. They are metabolized primarily in the liver and are then excreted by the kidneys. Some of the topical corticosteroids and their metabolites are also excreted into the bile.

INDICATIONS AND USAGE

Topical corticosteroids are indicated for relief of the inflammatory and pruritic manifestations of corticosteroid-responsive dermatoses.

CONTRAINDICATIONS

Topical steroids are contraindicated in those patients with a history of hypersensitivity to any of the components of the preparation.

PRECAUTIONS

General

Systemic absorption of topical corticosteroids has produced reversible hypothalamic-pituitary-adrenal (HPA) axis suppression, manifestations of Cushing's syndrome, hyperglycemia, and glucosuria in some patients.

Conditions which augment systemic absorption include the application of the more potent steroids, use over large surface areas, prolonged use, and the addition of occlusive dressings.

Therefore, patients receiving a large dose of a potent topical steroid applied to a large surface area or under an occlusive dressing should be evaluated periodically for evidence of HPA axis suppression by using the urinary free cortisol and ACTH stimulation tests. If HPA axis suppression is noted, an attempt should be made to withdraw the drug, to reduce the frequency of application, or to substitute a less potent steroid.

Recovery of HPA axis function is generally prompt and complete upon discontinuation of the drug. Infrequently, signs and symptoms of steroid withdrawal may occur, requiring supplemental systemic corticosteroids.

Pediatric patients may absorb proportionally larger amounts of topical corticosteroids and thus be more susceptible to systemic toxicity. (See PRECAUTIONS - Pediatric Use.)

If irritation develops, topical corticosteroids should be discontinued and appropriate therapy instituted.

In the presence of dermatological infections, the use of an appropriate antifungal or antibacterial agent should be instituted. If a favorable response does not occur promptly, the corticosteroid should be discontinued until the infection has been adequately controlled.

Information for the Patient

Patients using topical corticosteroids should receive the following information and instructions:

1. This medication is to be used as directed by the physician. It is for external use only. Avoid contact with the eyes.
2. Patients should be advised not to use this medication for any disorder other than for which it was prescribed.
3. The treated skin area should not be bandaged or otherwise covered or wrapped as to be occlusive unless directed by the physician.
4. Patients should report any signs of local adverse reactions especially under occlusive dressing.
5. Parents of pediatric patients should be advised not to use tight-fitting diapers or plastic pants on an infant or child being treated in the diaper area, as these garments may constitute occlusive dressings.

Laboratory Tests

The following tests may be helpful in evaluating the HPA axis suppression:

- Urinary free cortisol test
- ACTH stimulation test

Carcinogenesis, Mutagenesis, Impairment of Fertility

Long-term animal studies have not been performed to evaluate the carcinogenic potential or the effect on fertility of topical corticosteroids.

Studies to determine mutagenicity with prednisolone and hydrocortisone have revealed negative results.

Pregnancy Category C

Corticosteroids are generally teratogenic in laboratory animals when administered systemically at relatively low dosage levels. The more potent corticosteroids have been shown to be teratogenic after dermal application in laboratory animals. There are no adequate and well-controlled studies in pregnant women on teratogenic effects from topically applied corticosteroids. Therefore, topical corticosteroids should be used during pregnancy only if the potential benefit justifies the potential risk to the fetus. Drugs of this class should not be used extensively on pregnant patients, in large amounts, or for prolonged periods of time.

Nursing Mothers

It is not known whether topical administration of corticosteroids could result in sufficient systemic absorption to produce detectable quantities in breast milk. Systemically administered corticosteroids are secreted into breast milk in quantities notlikely to have a deleterious effect on the infant. Nevertheless, caution should be exercised when topical corticosteroids are administered to a nursing woman.

Pediatric Use

Safety and effectiveness of diflorasone diacetate ointment in pediatric patients have not been established. Because of a higher ratio of skin surface area to body mass, pediatric patients are at a greater risk than adults of HPA axis suppression when they are treated with topical corticosteroids. They are, therefore, also at greater risk of glucocorticosteroid insufficiency after withdrawal of treatment and of Cushing's syndrome while on treatment. Adverse effects including striae have been reported with inappropriate use of topical corticosteroids in pediatric patients.

HPA axis suppression, Cushing's syndrome, and intracranial hypertension have been reported in pediatric patients receiving topical corticosteroids. Manifestations of adrenal suppression in pediatric patients include linear growth retardation, delayed weight gain, low plasma cortisol levels, and absence of response to ACTH stimulation. Manifestations of intracranial hypertension include bulging fontanelles, headaches, and bilateral papilledema.

ADVERSE REACTIONS

The following local adverse reactions have been reported with topical corticosteroids, but may occur more frequently with the use of occlusive dressings. These reactions are listed in approximate decreasing order of occurrence:

1. Burning
2. Itching
3. Irritation
4. Dryness
5. Folliculitis
6. Hypertrichosis
7. Acneiform eruptions
8. Hypopigmentation
9. Perioral dermatitis
10. Allergic contact dermatitis
11. Maceration of the skin
12. Secondary infection
13. Skin atrophy
14. Striae
15. Miliaria

OVERDOSAGE

Topically applied corticosteroids can be absorbed in sufficient amounts to produce systemic effects. (See PRECAUTIONS.)

DOSAGE AND ADMINISTRATION

Diflorasone diacetate ointment should be applied to the affected area as a thin film from one to three times daily depending on the severity or resistant nature of the condition.

Occlusive dressings may be used for the management of psoriasis or recalcitrant conditions. If an infection develops, the use of occlusive dressings should be discontinued and appropriate antimicrobial therapy initiated.

HOW SUPPLIED

Diflorasone Diacetate Ointment USP, 0.05% is available in 15 gram (NDC 51672-1295-1), 30 gram (NDC 51672-1295-2) and 60 gram (NDC 51672-1295-3) tubes.

STORAGE AND HANDLING

Store at 20° to 25°C (68° to 77°F)[see USP Controlled Room Temperature].

Mfd. by: Taro Pharmaceuticals Inc., Brampton, Ontario, Canada L6T 1C1
Dist. by: Taro Pharmaceuticals U.S.A., Inc.,Hawthorne, NY 10532

Revised: May, 2015

PK-2578-2
0515-2
63

PRINCIPAL DISPLAY PANEL - 30 g Tube Carton

NDC 51672-1295-2

30 g

Diflorasone Diacetate
Ointment USP, 0.05%

FOR TOPICAL USE ONLY.
NOT FOR OPHTHALMIC USE.

Rx only

Keep this and all medications out of the reach of children.

TARO